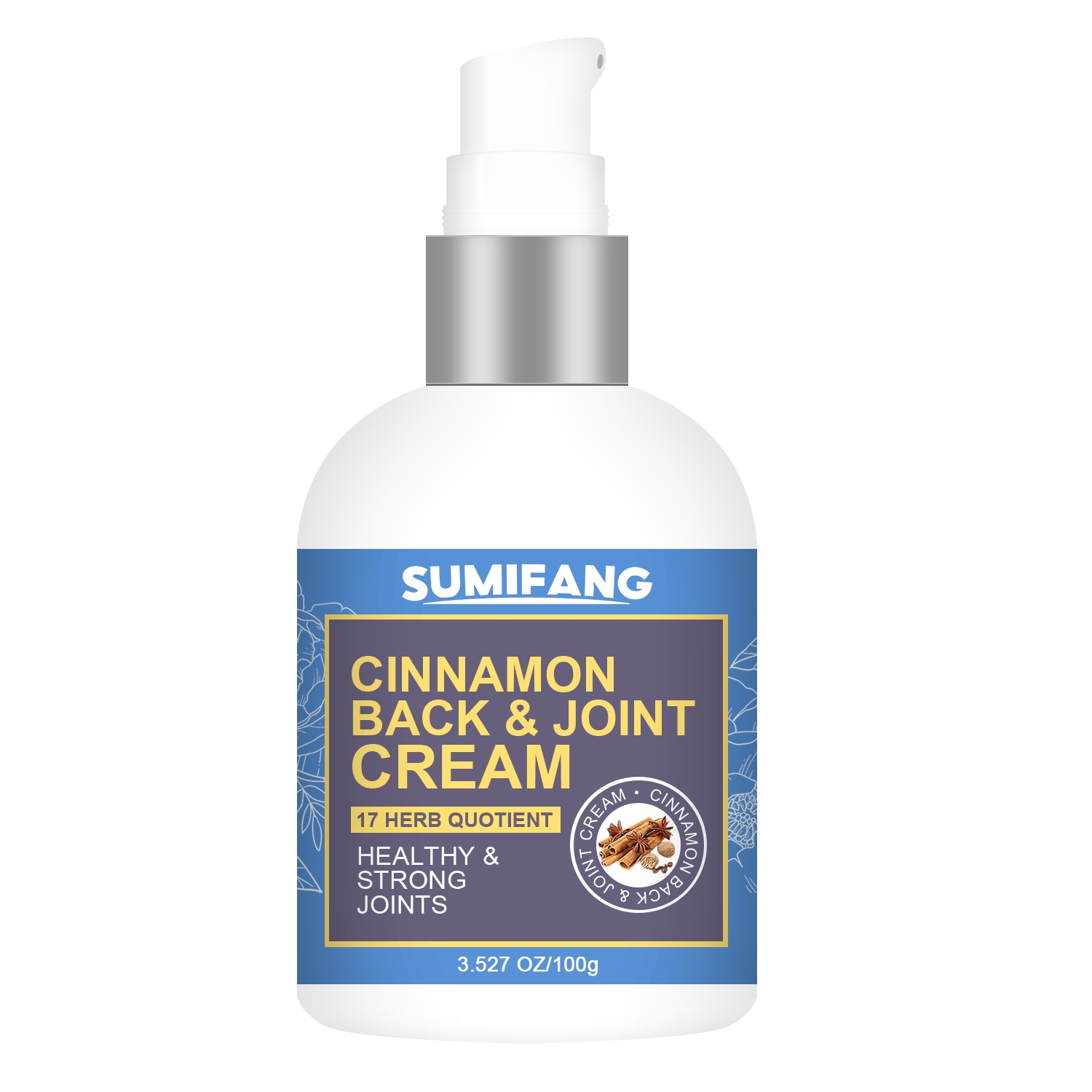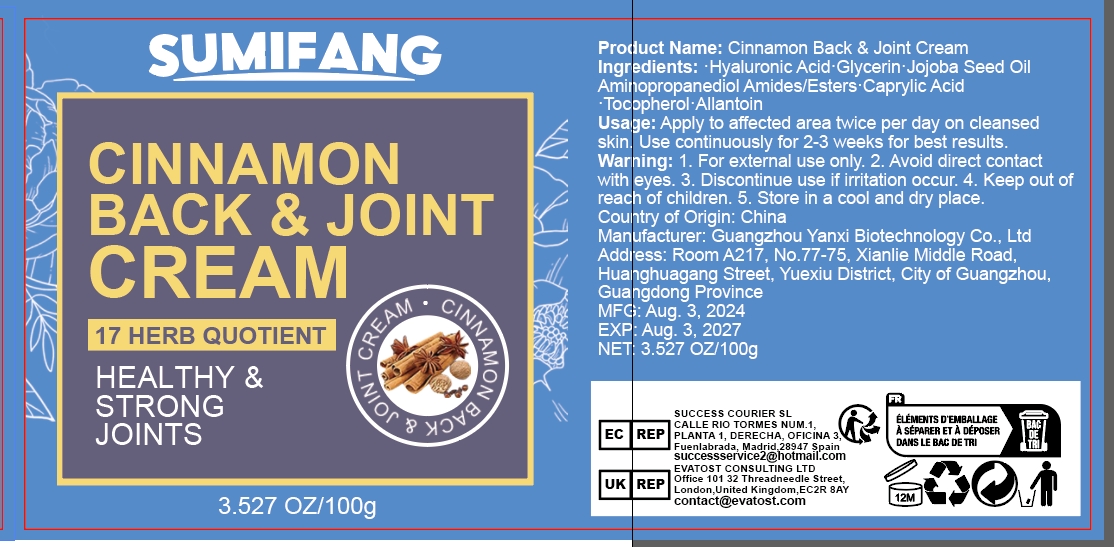 DRUG LABEL: CINNAMON BACK JOINTCREAM
NDC: 84025-116 | Form: CREAM
Manufacturer: Guangzhou Yanxi Biotechnology Co.. Ltd
Category: otc | Type: HUMAN OTC DRUG LABEL
Date: 20240805

ACTIVE INGREDIENTS: HYALURONIC ACID 5 mg/100 g; GLYCERIN 3 mg/100 g
INACTIVE INGREDIENTS: WATER

DOSAGE AND ADMINISTRATION

Cream for massaging body joints

WARNINGS

Keep out of children

INACTIVE INGREDIENT

Aqua

INDICATIONS AND USAGE

Relieves joints discomfort

Keep out of children

PURPOSE

Reduce joint discomfort and keep joints healthy